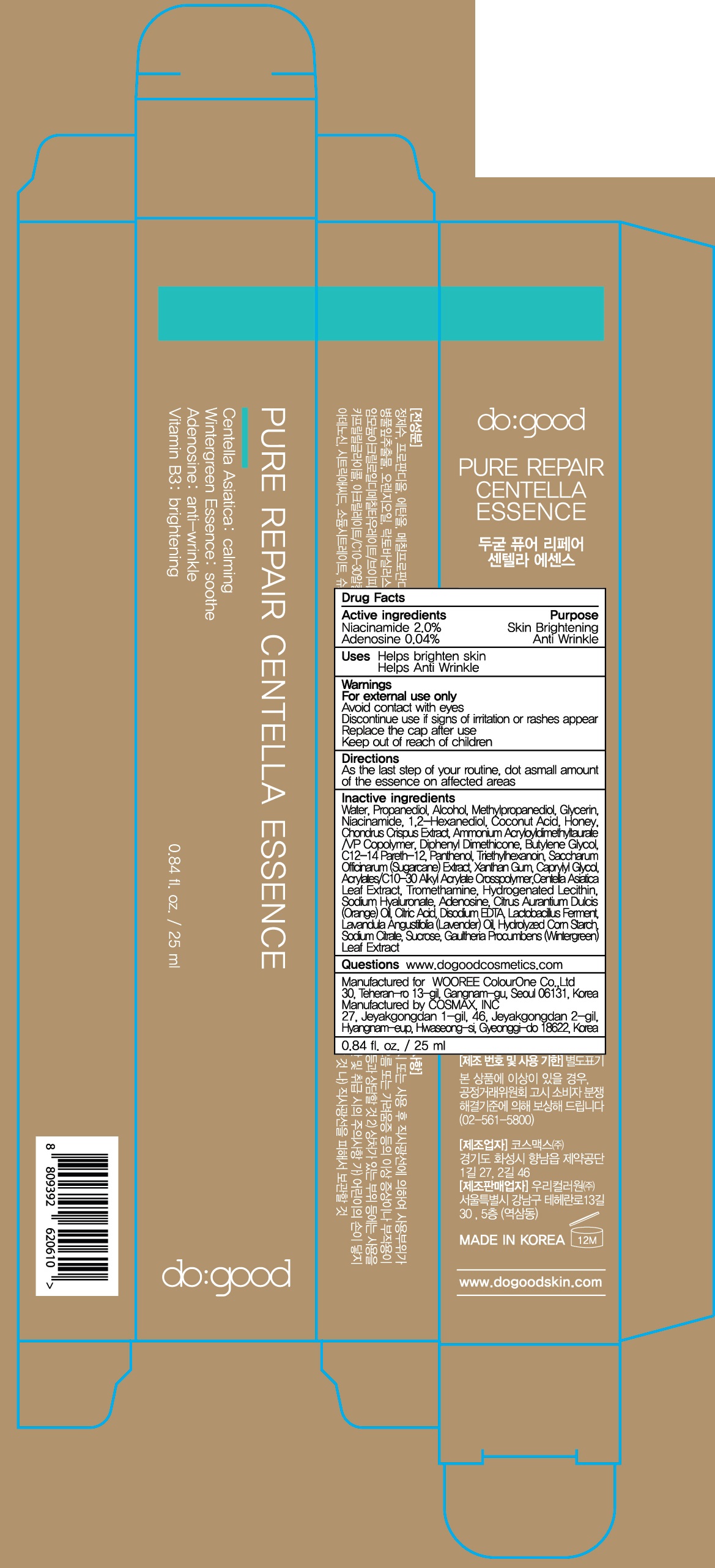 DRUG LABEL: do good Pure Repair Centella Essence
NDC: 72058-060 | Form: LIQUID
Manufacturer: WOOREE Colourone Co.,Ltd
Category: otc | Type: HUMAN OTC DRUG LABEL
Date: 20180226

ACTIVE INGREDIENTS: Niacinamide 0.5 g/25 mL; Adenosine 0.01 g/25 mL
INACTIVE INGREDIENTS: Water; Propanediol

ACTIVE INGREDIENT

Active ingredients: Niacinamide 2.0%, Adenosine 0.04%

INACTIVE INGREDIENT

Inactive ingredients:

Water, Propanediol, Alcohol, Methylpropanediol, Glycerin, 1,2-Hexanediol, Coconut Acid, Honey, Chondrus Crispus Extract, Saccharum Officinarum (Sugarcane) Extract, Centella Asiatica Leaf Extract, Citrus Aurantium Dulcis (Orange) Oil, Lactobacillus Ferment, Lavandula Angustifolia (Lavender) Oil, Hydrolyzed Corn Starch, Gaultheria Procumbens (Wintergreen) Leaf Extract, Ammonium Acryloyldimethyltaurate/VP Copolymer, Diphenyl Dimethicone, Butylene Glycol, C12-14 Pareth-12, Panthenol, Triethylhexanoin, Caprylyl Glycol, Acrylates/C10-30 Alkyl Acrylate Crosspolymer, Tromethamine, Hydrogenated Lecithin, Sodium Hyaluronate, Citric Acid, Sodium Citrate, Sucrose, Xanthan Gum, Disodium EDTA

PURPOSE

Purpose: Skin Brightening, Anti wrinkle

WARNINGS

For external use only.

Avoid contact with eyes.

Discontinue use if signs of irritation or rashes appear.

Replace the cap after use.

Keep out of reach of children

KEEP OUT OF REACH OF CHILDREN

Uses

- Helps brighten skin

- Helps Anti Wrinkle

Directions

As the last step of your routine, dot a small amount of the essence on affected areas.